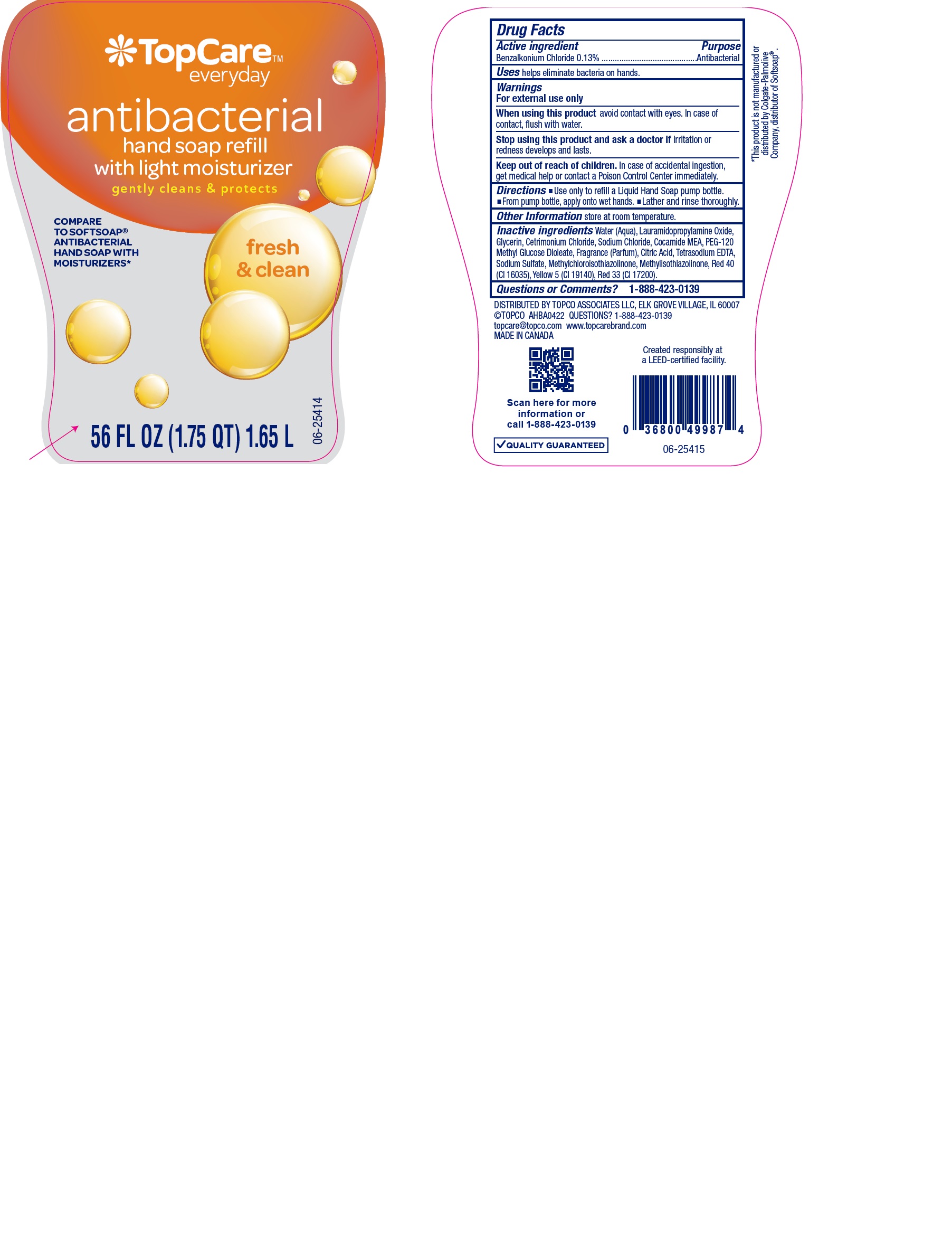 DRUG LABEL: Handsoap
NDC: 36800-535 | Form: SOAP
Manufacturer: Topco Associates LLC
Category: otc | Type: HUMAN OTC DRUG LABEL
Date: 20241019

ACTIVE INGREDIENTS: BENZALKONIUM CHLORIDE 130 mg/100 mL
INACTIVE INGREDIENTS: CITRIC ACID MONOHYDRATE; EDETATE SODIUM; METHYLISOTHIAZOLINONE; GLYCERIN; WATER; FD&C RED NO. 40; LAURAMIDOPROPYLAMINE OXIDE; CETRIMONIUM CHLORIDE; SODIUM CHLORIDE; COCO MONOETHANOLAMIDE; PEG-120 METHYL GLUCOSE DIOLEATE; METHYLCHLOROISOTHIAZOLINONE; FD&C YELLOW NO. 5; D&C RED NO. 33; SODIUM SULFATE

Topcare Antibacterial Hand Soap.

ACTIVE INGREDIENT

Benzalkonium Chloride

PURPOSE

Handwashing

WARNINGS

For External Use only

WHEN USING

Avoid contact with eyes. In case of contact, flush with water

STOP USE

Stop using this product and ask a doctor if irritation or redness develops and lasts.

KEEP OUT OF REACH OF CHILDREN

In case of accidental ingestion, get medical help or contact a Poison Control Center immediately

Directions

. Use only to refill a Liquid Hand Soap pump bottle.
. From pump bottle, apply onto wet hands.
. Lather and rinse thoroughly.

Dosage Section

Topical use only. Use when required.

STORAGE AND HANDLING

Store at room temperature

INACTIVE INGREDIENT

Water (Aqua), Lauramidopropylamine Oxide, Glycerin, Cetrimonium Chloride, Sodium Chloride, Cocamide MEA, PEG-120 Methyl Glucose Dioleate, Fragrance (Parfum), Citric Acid, Tetrasodium EDTA, Sodium Sulfate, Methylchloroisothiazolinone, Methylisothiazolinone, Red 40 (CI 16035), Yellow 5 (CI 19140), Red 33 (CI 17200).